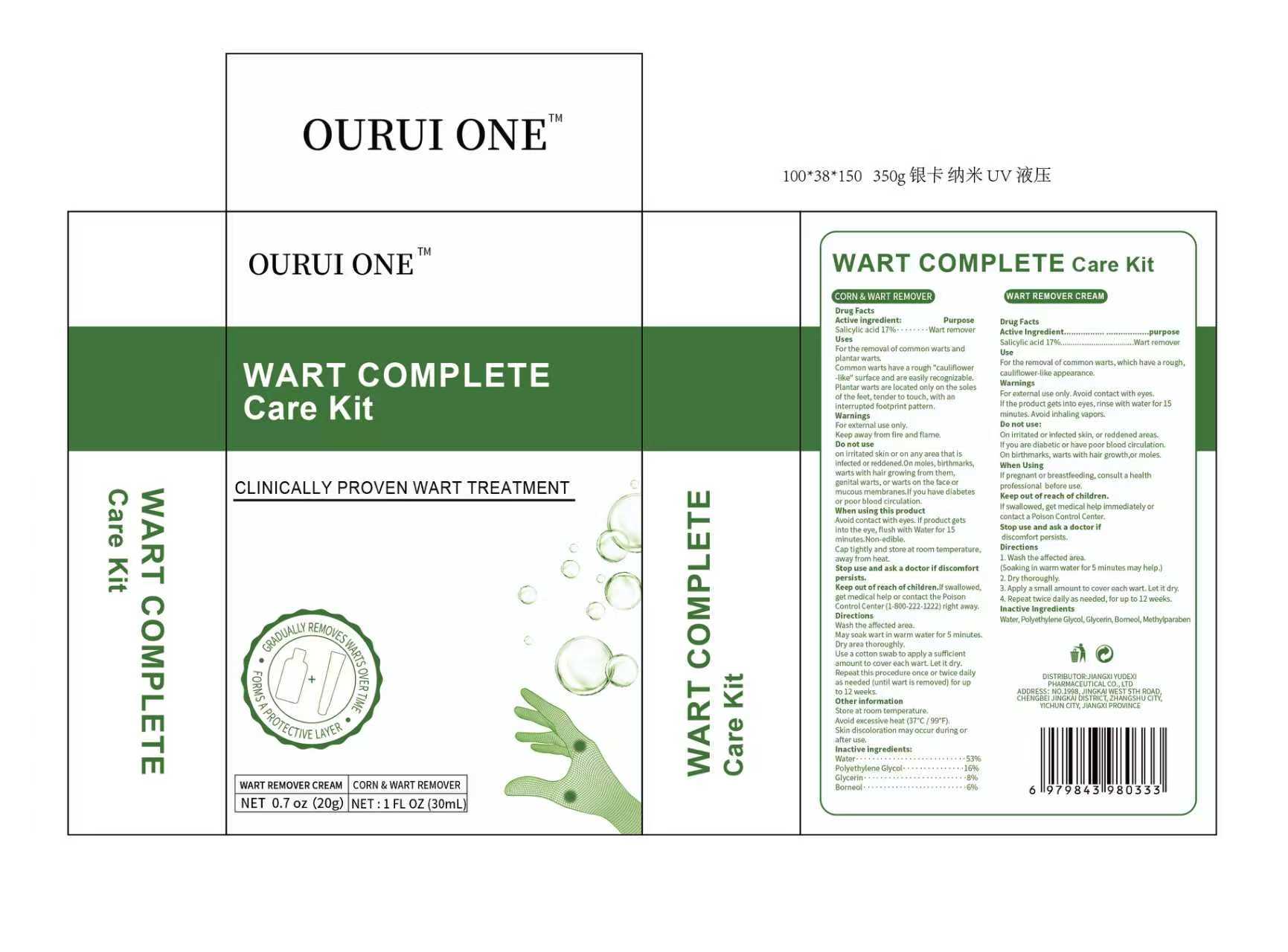 DRUG LABEL: OURUI ONE WART COMPLETE Care Kit CORN WART REMOVER
NDC: 85248-086 | Form: CREAM
Manufacturer: Jiangxi Yudexi Pharmaceutical Co., LTD
Category: otc | Type: HUMAN OTC DRUG LABEL
Date: 20260209

ACTIVE INGREDIENTS: SALICYLIC ACID 17 g/100 g
INACTIVE INGREDIENTS: METHYLPARABEN; WATER; BORNEOL; GLYCERIN; POLYETHYLENE GLYCOL, UNSPECIFIED

85248-086
85248-087

Active Ingredient

CORN & WART REMOVER：
Salicylic acid 17%
WART REMOVER CREAM：
Salicylic acid 17%

Purpose

CORN & WART REMOVER：
Wart remover
WART REMOVER CREAM：
Wart remover

Use

CORN & WART REMOVER：
For the removal of common warts and plantar warts.Common warts have a rough"cauliflower-like" surface and are easily recognizable.Plantar warts are located only on the soles of the feet, tender to touch, with an interrupted footprint pattern.
WART REMOVER CREAM：
For the removal of common warts, which have a rough,cauliflower-like appearance.

Warnings

CORN & WART REMOVER：
For external use only.
Keep away from fire and flame.
WART REMOVER CREAM：
For external use only.Avoid contact with eyes. If the product gets into eyes, rinse with water for 15 minutes. Avoid inhaling vapors.

Do not use

CORN & WART REMOVER：
on irritated skin or on any
area that is infected or reddened·on
moles, birthmarks, warts with hair
growing from them, genital warts or
warts on the face or mucous membranes.
If you have diabetes or poor blood
circulation.
WART REMOVER CREAM：
On irritated or infected skin, or reddened areas. If you are diabetic or have poor blood circulation. On birthmarks, warts with hair growth,or moles.

When Using

CORN & WART REMOVER：
Avoid contact with eyes. lf product gets into the eye, flush with Water for 15 minutes.Non-edible. Cap tightly and store at room temperature, away from heat.
WART REMOVER CREAM：
If pregnant or breastfeeding, consult a health professional before use.

Stop Use

CORN & WART REMOVER：
Stop use and ask a doctor if
discomfort persists.
WART REMOVER CREAM：
Stop use and ask a doctor if discomfort persists.

Ask Doctor

CORN & WART REMOVER：
Stop use and ask a doctor if
discomfort persists.
WART REMOVER CREAM：
Stop use and ask a doctor if discomfort persists.

Keep Oot Of Reach Of Children

CORN & WART REMOVER：
If swallowed, get medical help or
contact the Poison Control Center
(1-800-222-1222) right away.
WART REMOVER CREAM：
If swallowed, get medical help immediately or contact a Poison Control Center.

Directions

CORN & WART REMOVER：
Wash the affected area.May soak wart in warm water for 5 minutes. Dry area thoroughly.
Use a cotton swab to apply a sufficient amount to cover each wart. Let it dry.Repeat this procedure once or twice daily as needed (until wart is removed) for up to 12 weeks.
WART REMOVER CREAM：
1.Wash the affected area.
(Soaking in warm water for 5 minutes may help.) 2. Dry thoroughly. 3. Apply a small amount to cover each wart. Let it dry. 4. Repeat twice daily as needed, for up to 12 weeks.

Other information

CORN & WART REMOVER：
Store at room temperature.Avoid excessive heat (37°C/ 99°F).Skin discoloration may occur during or after use.

Inactive ingredients

CORN & WART REMOVER：
Water，Polyethylene Glycol，Glycerin，Borneol，
WART REMOVER CREAM：
Water, Polyethylene Glycol, Glycerin, Borneol，Methylparaben.